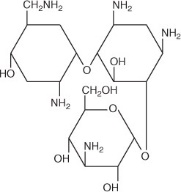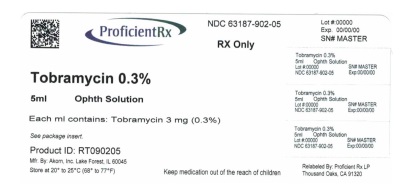 DRUG LABEL: Tobramycin
NDC: 63187-902 | Form: SOLUTION/ DROPS
Manufacturer: Proficient Rx LP
Category: prescription | Type: HUMAN PRESCRIPTION DRUG LABEL
Date: 20191101

ACTIVE INGREDIENTS: Tobramycin 3 mg/1 mL
INACTIVE INGREDIENTS: Boric Acid; Sodium Chloride; sodium Sulfate; Tyloxapol; Sodium Hydroxide; Sulfuric Acid; WATER; Benzalkonium Chloride

Tobramycin Ophthalmic Solution, USP
0.3%–Sterile

Rx only

DESCRIPTION:

Tobramycin Ophthalmic Solution USP, 0.3% is a sterile topical ophthalmic antibiotic formulation prepared specifically for topical therapy of external ophthalmic infections.

Tobramycin is a water soluble aminoglycoside antibiotic active against a wide variety of gram-negative and gram-positive ophthalmic pathogens. The molecular formula is C18H37N5O9, the molecular weight is 467.52 and the structural formula is:

Chemical Name:

O-{3-amino-3-deoxy-α-D-gluco-pyranosyl-(1 → 4)}-O-{2,6-diamino-2,3,6-trideoxy-α-D-ribohexo-pyranosyl-(1 → 6)}-2- deoxystreptamine.

Each mL contains:

Active: Tobramycin 3 mg (0.3%). Inactives: Boric Acid, Sodium Chloride, Sodium Sulfate, Tyloxapol, Sodium Hydroxide and/or Sulfuric Acid to adjust pH (7.0 to 8.0), and Purified Water USP. Preservative: Benzalkonium Chloride 0.1 mg (0.01%).

CLINICAL PHARMACOLOGY:

In Vitro Data: In Vitro studies have demonstrated tobramycin is active against susceptible strains of the following microorganisms:

Staphylococci, including S. aureus and S. epidermidis (coagulase-positive and coagulase-negative), including penicillin-resistant strains.

Streptococci, including some of the Group A betahemolytic species, some nonhemolytic species, and some Streptococcus pneumoniae.

Pseudomonas aeruginosa, Escherichia coli, Klebsiella pneumoniae, Enterobacter aerogenes, Proteus mirabilis, Morganella morganii, most Proteus vulgaris strains, Haemophilus influenzae and H. aegyptius, Moraxella lacunata, Acinetobacter calcoaceticus and some Neisseria species.

Bacterial susceptibility studies demonstrate that in some cases, microorganisms resistant to gentamicin retain susceptibility to tobramycin.

INDICATIONS AND USAGE:

Tobramycin Ophthalmic Solution USP, 0.3% is a topical antibiotic indicated in the treatment of external infections of the eye and its adnexa caused by susceptible bacteria. Appropriate monitoring of bacterial response to topical antibiotic therapy should accompany the use of Tobramycin Ophthalmic Solution USP, 0.3%. Clinical studies have shown tobramycin to be safe and effective for use in pediatric patients.

CONTRAINDICATIONS:

Tobramycin Ophthalmic Solution USP, 0.3% is contraindicated in patients with known hypersensitivity to any of its components.

WARNINGS:

FOR TOPICAL OPHTHALMIC USE ONLY. NOT FOR INJECTION INTO THE EYE. Sensitivity to topically applied aminoglycosides may occur in some patients. If a sensitivity reaction to Tobramycin Ophthalmic Solution USP, 0.3% occurs, discontinue use.

PRECAUTIONS:

General:

As with other antibiotic preparations, prolonged use may result in overgrowth of nonsusceptible organisms, including fungi. If superinfection occurs, appropriate therapy should be initiated. Cross-sensitivity to other aminoglycoside antibiotics may occur; if hypersensitivity develops with this product, discontinue use and institute appropriate therapy. Patients should be advised not to wear contact lenses if they have signs and symptoms of bacterial conjunctivitis.

PATIENT COUNSELING INFORMATION

Information for Patients: Do not touch dropper tip to any surface, as this may contaminate the solution.

PREGNANCY

Pregnancy Category B: Reproduction studies in three types of animals at doses up to thirty-three times the normal human systemic dose have revealed no evidence of impaired fertility or harm to the fetus due to tobramycin. There are, however, no adequate and wellcontrolled studies in pregnant women. Because animal studies are not always predictive of human response, this drug should be used during pregnancy only if clearly needed.

NURSING MOTHERS

Nursing Mothers: Because of the potential for adverse reactions in nursing infants from tobramycin, a decision should be made whether to discontinue nursing the infant or discontinue the drug, taking into account the importance of the drug to the mother.

PEDIATRIC USE

Pediatric Use: Safety and effectiveness in pediatric patients below the age of two months has not been established.

GERIATRIC USE

Geriatric Use: No overall clinical differences in safety or effectiveness have been observed between the elderly and other adult patients.

ADVERSE REACTIONS:

The most frequent adverse reactions to tobramycin ophthalmic solution are hypersensitivity and localized ocular toxicity, including lid itching and swelling, and conjunctival erythema. These reactions occur in less than three of 100 patients treated with tobramycin. Similar reactions may occur with the topical use of other aminoglycoside antibiotics. Other adverse reactions have not been reported from tobramycin therapy; however, if topical ocular tobramycin is administered concomitantly with systemic aminoglycoside antibiotics, care should be taken to monitor the total serum concentration.

OVERDOSAGE:

Clinically apparent signs and symptoms of an overdose of tobramycin ophthalmic solution (punctate keratitis, erythema, increased lacrimation, edema and lid itching) may be similar to adverse reaction effects seen in some patients.

DOSAGE AND ADMINISTRATION:

In mild to moderate disease, instill one or two drops into the affected eye(s) every four hours. In severe infections, instill two drops into the eye(s) hourly until improvement, following which treatment should be reduced prior to discontinuation.

HOW SUPPLIED:

Tobramycin Ophthalmic Solution USP, 0.3% is supplied as a sterile solution in plastic dropper bottles in two sizes:

NDC 63187-902-02. . . . . . . . . . . . 2 mL

NDC 63187-902-05. . . . . . . . . . . . 5 mL

STORAGE:

Store at 20° to 25°C (68° to 77°F) [see USP Controlled Room Temperature]. Keep container tightly closed.

Protect from excessive heat.

Akorn
Manufactured by: Akorn, Inc.
Lake Forest, IL 60045

Relabeled by: Proficient Rx LP
Thousand Oaks, CA 91320

GTM00N
Rev. 11/11

Principal Display Panel Text for Container Label:

NDC 63187-902-05

Tobramycin

Ophthalmic

Solution, USP

0.3%

5 mL

Sterile

Rx only